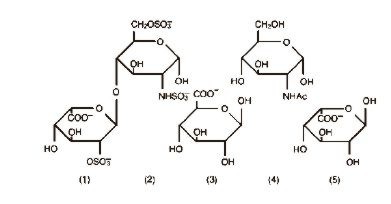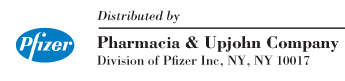 DRUG LABEL: Unknown
Category: prescription | Type: HUMAN PRESCRIPTION DRUG LABELING
Date: 20060413

Heparin Sodium
Injection, USP

from beef lung

DESCRIPTION

Heparin is a heterogenous group of straight-chain anionic mucopolysaccharides, called glycosaminoglycans having anticoagulant properties. Although others may be present, the main sugars occurring in heparin are: (1) α-L-iduronic acid 2-sulfate, (2) 2-deoxy-2-sulfamino-α-D-glucose 6-sulfate, (3) β-D-glucuronic acid, (4) 2-acetamido-2-deoxy-α-D-glucose, and (5) α-L-iduronic acid. These sugars are present in decreasing amounts, usually in the order (2) > (1) > (4) > (3) > (5), and are joined by glycosidic linkages, forming polymers of varying sizes. Heparin is strongly acidic because of its content of covalently linked sulfate and carboxylic acid groups. In heparin sodium, the acidic protons of the sulfate units are partially replaced by sodium ions.

Structure of Heparin Sodium (representative subunits):

Heparin Sodium Injection, USP is a sterile solution of heparin sodium derived from bovine lung tissue, standardized for anticoagulant activity. It is to be administered by intravenous or deep subcutaneous routes. The potency is determined by a biological assay using a USP reference standard based on units of heparin activity per milligram. Heparin is pyrogen-free.

Each mL of the 1,000 and 5,000 USP Units per mL preparations contains: heparin sodium 1,000 or 5,000 USP Units; 9 mg sodium chloride; 9.45 mg benzyl alcohol added as preservative. Each mL of the 10,000 USP Units per mL preparations contains: heparin sodium 10,000 USP Units; 9.45 mg benzyl alcohol added as preservative.

When necessary, the pH of Heparin Sodium Injection, USP was adjusted with hydrochloric acid and/or sodium hydroxide. The pH range is 5.0–7.5.

CLINICAL PHARMACOLOGY

Heparin inhibits reactions that lead to the clotting of blood and the formation of fibrin clots both in vitro and in vivo. Heparin acts at multiple sites in the normal coagulation system. Small amounts of heparin in combination with antithrombin III (heparin cofactor) can inhibit thrombosis by inactivating activated Factor X and inhibiting the conversion of prothrombin to thrombin. Once active thrombosis has developed, larger amounts of heparin can inhibit further coagulation by inactivating thrombin and preventing the conversion of fibrinogen to fibrin. Heparin also prevents the formation of a stable fibrin clot by inhibiting the activation of the fibrin stabilizing factor.

Bleeding time is usually unaffected by heparin. Clotting time is prolonged by full therapeutic doses of heparin; in most cases, it is not measurably affected by low doses of heparin.

Patients over 60 years of age, following similar doses of heparin, may have higher plasma levels of heparin and longer activated partial thromboplastin times (APTTs) compared with patients under 60 years of age.

Peak plasma levels of heparin are achieved 2–4 hours following subcutaneous administration, although there are considerable individual variations. Loglinear plots of heparin plasma concentrations with time for a wide range of dose levels are linear which suggests the absence of zero order processes. Liver and the reticulo-endothelial system are the site of biotransformation. The biphasic elimination curve, a rapidly declining alpha phase (t½=10 minutes) and after the age of 40 a slower beta phase, indicates uptake in organs. The absence of a relationship between anticoagulant half-life and concentration half-life may reflect factors such as protein binding of heparin.

Heparin does not have fibrinolytic activity; therefore, it will not lyse existing clots.

INDICATIONS AND USAGE

Heparin Sodium Injection is indicated for:

Anticoagulant therapy in prophylaxis and treatment of venous thrombosis and its extension;

(In a low-dose regimen) for prevention of postoperative deep venous thrombosis and pulmonary embolism in patients undergoing major abdomino-thoracic surgery or who for other reasons are at risk of developing thromboembolic disease (see DOSAGE AND ADMINISTRATION);

Prophylaxis and treatment of pulmonary embolism;

Atrial fibrillation with embolization;

Diagnosis and treatment of acute and chronic consumption coagulopathies (disseminated intravascular coagulation);

Prevention of clotting in arterial and heart surgery;

Prophylaxis and treatment of peripheral arterial embolism;

As an anticoagulant in blood transfusions, extracorporeal circulation, and dialysis procedures and in blood samples for laboratory purposes.

CONTRAINDICATIONS

Heparin sodium should not be used in patients:

With severe thrombocytopenia;

In whom suitable blood coagulation tests—e.g., the whole-blood clotting time, partial thromboplastin time, etc.—cannot be performed at appropriate intervals (this contraindication refers to full-dose heparin; there is usually no need to monitor coagulation parameters in patients receiving low-dose heparin);

With an uncontrollable active bleeding state (see WARNINGS), except when this is due to disseminated intravascular coagulation.

WARNINGS

Heparin is not intended for intramuscular use.

Hypersensitivity

Patients with documented hypersensitivity to heparin should be given the drug only in clearly life-threatening situations.

Hemorrhage

Hemorrhage can occur at virtually any site in patients receiving heparin. An unexplained fall in hematocrit, fall in blood pressure, or any other unexplained symptom should lead to serious consideration of a hemorrhagic event.

Heparin sodium should be used with extreme caution in disease states in which there is increased danger of hemorrhage. Some of the conditions in which increased danger of hemorrhage exists are:

Cardiovascular—Subacute bacterial endocarditis. Severe hypertension.

Surgical—During and immediately following (a) spinal tap or spinal anesthesia or (b) major surgery, especially involving the brain, spinal cord, or eye.

Hematologic—Conditions associated with increased bleeding tendencies, such as hemophilia, thrombocytopenia, and some vascular purpuras.

The anticoagulant effect of heparin is enhanced by concurrent treatment with antithrombin III (human) in patients with hereditary antithrombin III deficiency. Thus in order to avoid bleeding, reduced dosage of heparin is recommended during treatment with antithrombin III (human).

Gastrointestinal—Ulcerative lesions and continuous tube drainage of the stomach or small intestine.

Other—Menstruation, liver disease with impaired hemostasis.

Coagulation Testing

When heparin sodium is administered in therapeutic amounts, its dosage should be regulated by frequent blood coagulation tests. If the coagulation test is unduly prolonged or if hemorrhage occurs, heparin sodium should be discontinued promptly (see OVERDOSAGE).

Thrombocytopenia

Thrombocytopenia has been reported to occur in patients receiving heparin with a reported incidence of 0 to 30%. Mild thrombocytopenia (count greater than 100,000/mm^3) may remain stable or reverse even if heparin is continued. However, reduction in platelet count of any degree should be monitored closely. If the count falls below 100,000/mm^3 or if recurrent thrombosis develops (see White Clot Syndrome, PRECAUTIONS), the heparin product should be discontinued. If continued heparin therapy is essential, administration of heparin from a different organ source can be reinstituted with caution.

Miscellaneous

This product contains benzyl alcohol as preservative. Benzyl alcohol has been reported to be associated with a fatal "Gasping Syndrome" in premature infants.

PRECAUTIONS

1. General

a. White Clot Syndrome

It has been reported that patients on heparin may develop new thrombus formation in association with thrombocytopenia resulting from irreversible aggregation of platelets induced by heparin, the so-called "white clot syndrome." The process may lead to severe thromboembolic complications like skin necrosis, gangrene of the extremities that may lead to amputation, myocardial infarction, pulmonary embolism, stroke, and possibly death. Therefore, heparin administration should be promptly discontinued if a patient develops new thrombosis in association with a reduction in platelet count.

b. Heparin Resistance

Increased resistance to heparin is frequently encountered in fever, thrombosis, thrombophlebitis, infections with thrombosing tendencies, myocardial infarction, cancer, in postsurgical patients, and patients with antithrombin III deficiency.

c. Increased Risk to Older Patients, Especially Women

A higher incidence of bleeding has been reported in patients, particularly women, over 60 years of age.

2. Laboratory Tests

Periodic platelet counts, hematocrits, and tests for occult blood in stool are recommended during the entire course of heparin therapy, regardless of the route of administration (see DOSAGE AND ADMINISTRATION).

3. Drug Interactions

a. Drugs Enhancing Heparin Effect

Oral anticoagulants

Heparin sodium may prolong the one-stage prothrombin time. Therefore, when heparin sodium is given with dicumarol or warfarin sodium, a period of at least 5 hours after the last intravenous dose or 24 hours after the last subcutaneous dose should elapse before blood is drawn if a valid prothrombin time is to be obtained.

Platelet inhibitors

Drugs such as acetylsalicylic acid, dextran, phenylbutazone, ibuprofen, indomethacin, dipyridamole, hydroxychloroquine and others that interfere with platelet-aggregation reactions (the main hemostatic defense of heparinized patients) may induce bleeding and should be used with caution in patients receiving heparin sodium.

The anticoagulant effect of heparin is enhanced by concurrent treatment with antithrombin III (human) in patients with hereditary antithrombin III deficiency. Thus in order to avoid bleeding, reduced dosage of heparin is recommended during treatment with antithrombin III (human).

b. Drugs Decreasing Heparin Effect

Digitalis, tetracyclines, nicotine, or antihistamines may partially counteract the anticoagulant action of heparin sodium. Heparin Sodium Injection should not be mixed with doxorubicin, droperidol, ciprofloxacin, or mitoxantrone, since it has been reported that these drugs are incompatible with heparin and a precipitate may form.

4. Drug/Laboratory Tests Interactions

Hyperaminotransferasemia

Significant elevations of aminotransferase (SGOT [S-AST] and SGPT [S-ALT]) levels have occurred in a high percentage of patients (and healthy subjects) who have received heparin. Since aminotransferase determinations are important in the differential diagnosis of myocardial infarction, liver disease, and pulmonary emboli, rises that might be caused by drugs (like heparin) should be interpreted with caution.

5. Carcinogenesis, Mutagenesis, Impairment of Fertility

No long-term studies in animals have been performed to evaluate carcinogenic potential of heparin. Also, no reproduction studies in animals have been performed concerning mutagenesis or impairment of fertility.

6. Pregnancy

Teratogenic Effects

Pregnancy Category C

Animal reproduction studies have not been conducted with heparin sodium. It is also not known whether heparin sodium can cause fetal harm when administered to a pregnant woman or can affect reproduction capacity. Heparin sodium should be given to a pregnant woman only if clearly needed.

Nonteratogenic Effects

Heparin does not cross the placental barrier.

7. Nursing Mothers

Heparin is not excreted in human milk.

8. Pediatric Use

See DOSAGE AND ADMINISTRATION.

9. Geriatric Use

A higher incidence of bleeding has been reported in patients over 60 years of age, especially women (see PRECAUTIONS, General). Clinical studies indicated that lower doses of heparin may be indicated in these patients (see CLINICAL PHARMACOLOGY and DOSAGE AND ADMINISTRATION).

ADVERSE REACTIONS

1. Hemorrhage

Hemorrhage is the chief complication that may result from heparin therapy (see WARNINGS). An overly prolonged clotting time or minor bleeding during therapy can usually be controlled by withdrawing the drug (see OVERDOSAGE). It should be appreciated that gastrointestinal or urinary tract bleeding during anticoagulant therapy may indicate the presence of an underlying occult lesion. Bleeding can occur at any site but certain specific hemorrhagic complications may be difficult to detect:

1. Adrenal hemorrhage, with resultant acute adrenal insufficiency, has occurred during anticoagulant therapy. Therefore, such treatment should be discontinued in patients who develop signs and symptoms of acute adrenal hemorrhage and insufficiency. Initiation of corrective therapy should not depend on laboratory confirmation of the diagnosis, since any delay in an acute situation may result in the patient's death.
2. Ovarian (corpus luteum) hemorrhage developed in a number of women of reproductive age receiving short- or long-term anticoagulant therapy. This complication if unrecognized may be fatal.
3. Retroperitoneal hemorrhage.

2. Local irritation

Local irritation, erythema, mild pain, hematoma or ulceration may follow deep subcutaneous (intrafat) injection of heparin sodium. These complications are much more common after intramuscular use, and such use is not recommended.

3. Hypersensitivity

Generalized hypersensitivity reactions have been reported, with chills, fever, and urticaria as the most usual manifestations, and asthma, rhinitis, lacrimation, headache, nausea and vomiting, and anaphylactoid reactions, including shock, occurring more rarely. Itching and burning, especially on the plantar site of the feet, may occur.

Thrombocytopenia has been reported to occur in patients receiving heparin with a reported incidence of 0–30%. While often mild and of no obvious clinical significance, a reduction in platelet count can be accompanied by severe thromboembolic complications such as skin necrosis, gangrene of the extremities that may lead to amputation, myocardial infarction, pulmonary embolism, stroke, and possibly death. (See WARNINGS, PRECAUTIONS.)

Certain episodes of painful, ischemic, and cyanosed limbs have in the past been attributed to allergic vasospastic reactions. Whether these are in fact identical to the thrombocytopenia associated complications remains to be determined.

4. Miscellaneous

Osteoporosis following long-term administration of high-doses of heparin, cutaneous necrosis after systemic administration, suppression of aldosterone synthesis, delayed transient alopecia, priapism, and rebound hyperlipemia on discontinuation of heparin sodium have also been reported.

Significant elevations of aminotransferase (SGOT [S-AST] and SGPT [S-ALT]) levels have occurred in a high percentage of patients (and healthy subjects) who have received heparin.

OVERDOSAGE

Symptoms

Bleeding is the chief sign of heparin overdosage. Nosebleeds, blood in urine or tarry stools may be noted as the first sign of bleeding. Easy bruising or petechial formations may precede frank bleeding.

Treatment

Neutralization of heparin effect. When clinical circumstances (bleeding) require reversal of heparinization, protamine sulfate (1% solution) by slow infusion will neutralize heparin sodium. No more than 50 mg should be administered, very slowly, in any 10 minute period. Each mg of protamine sulfate neutralizes approximately 100 USP heparin units. The amount of protamine required decreases over time as heparin is metabolized. Although the metabolism of heparin is complex, it may, for the purpose of choosing a protamine dose, be assumed to have a half-life of about ½ hour after intravenous injection.

Administration of protamine sulfate can cause severe hypotensive and anaphylactoid reactions. Because fatal reactions often resembling anaphylaxis have been reported, the drug should be given only when resuscitation techniques and treatment of anaphylactoid shock are readily available.

For additional information the labeling of Protamine Sulfate Injection, USP products should be consulted.

DOSAGE AND ADMINISTRATION

Parenteral drug products should be inspected visually for particulate matter and discoloration prior to administration, whenever solution and container permit. Slight discoloration does not alter potency.

When heparin is added to an infusion solution for continuous intravenous administration, the container should be inverted at least six times to ensure adequate mixing and prevent pooling of the heparin in the solution.

Heparin sodium is not effective by oral administration and should be given by intermittent intravenous injection, intravenous infusion, or deep subcutaneous (intrafat, i.e., above the iliac crest or abdominal fat layer) injection. The intramuscular route of administration should be avoided because of the frequent occurrence of hematoma at the injection site.

The dosage of heparin sodium should be adjusted according to the patient's coagulation test results. When heparin is given by continuous intravenous infusion, the coagulation time should be determined approximately every 4 hours in the early stages of treatment. When the drug is administered intermittently by intravenous injection, coagulation tests should be performed before each injection during the early stages of treatment and at appropriate intervals thereafter. Dosage is considered adequate when the activated partial thromboplastin time (APTT) is 1.5 to 2 times normal or when the whole blood clotting time is elevated approximately 2.5 to 3 times the control value. After deep subcutaneous (intrafat) injections, tests for adequacy of dosage are best performed on samples drawn 4–6 hours after the injections.

Periodic platelet counts, hematocrits, and tests for occult blood in stool are recommended during the entire course of heparin therapy, regardless of the route of administration.

Heparin Sodium Injection should not be mixed with doxorubicin, droperidol, ciprofloxacin, or mitoxantrone, since it has been reported that these drugs are incompatible with heparin and a precipitate may form.

Converting to Oral Anticoagulant

When an oral anticoagulant of the coumarin or similar type is to be begun in patients already receiving heparin sodium, baseline and subsequent tests of prothrombin activity must be determined at a time when heparin activity is too low to affect the prothrombin time. This is about 5 hours after the last I.V. bolus and 24 hours after the last subcutaneous dose. If continuous I.V. heparin infusion is used, prothrombin time can usually be measured at any time.

In converting from heparin to an oral anticoagulant, the dose of the oral anticoagulant should be the usual initial amount and thereafter prothrombin time should be determined at the usual intervals. To ensure continuous anticoagulation, it is advisable to continue full heparin therapy for several days after the prothrombin time has reached the therapeutic range. Heparin therapy may then be discontinued without tapering.

Therapeutic Anticoagulant Effect with Full-Dose Heparin

Although dosage must be adjusted for the individual patient according to the results of suitable laboratory tests, the following dosage schedules may be used as guidelines:

METHOD OF ADMINISTRATION | FREQUENCY | RECOMMENDED DOSE [Based on 150-lb. (68-kg) patient.]
Deep Subcutaneous (Intrafat) Injection | Initial Dose | 5,000 units by I.V. injection, followed by 10,000–20,000 units of a concentrated solution, subcutaneously
A different site should
be used for each injection to prevent the development of massive hematoma. | Every 8 hours or | 8,000–10,000 units of a concentrated solution
 | Every 12 hours | 15,000–20,000 units of a concentrated solution
Intermittent Intravenous Injection | Initial Dose | 10,000 units, either undiluted or in 50–100 mL of 0.9% Sodium Chloride Injection, USP
 | Every 4 to 6 hours | 5,000–10,000 units, either undiluted or in 50–100 mL of 0.9% Sodium Chloride Injection, USP
Continuous Intravenous Infusion | Initial Dose | 5,000 units by I.V. injection
 | Continuous | 20,000–40,000 units/24 hours in 1,000 mL of 0.9% Sodium Chloride Injection, USP (or in any compatible solution) for infusion

Pediatric Use

Follow recommendations of appropriate pediatric reference texts. In general, the following dosage schedule may be used as a guideline:

Initial Dose: 50 units/kg (I.V., drip)

Maintenance Dose: 100 units/kg (I.V., drip) every four hours, or
20,000 units/M^2/24 hours continuously

Geriatric Use

Patients over 60 years of age may require lower doses of heparin.

Surgery of the Heart and Blood Vessels

Patients undergoing total body perfusion for open-heart surgery should receive an initial dose of not less than 150 units of heparin sodium per kilogram of body weight. Frequently, a dose of 300 units per kilogram is used for procedures estimated to last less than 60 minutes or 400 units per kilogram for those estimated to last longer than 60 minutes.

Low-Dose Prophylaxis of Postoperative Thromboembolism

A number of well-controlled clinical trials have demonstrated that low-dose heparin prophylaxis, given just prior to and after surgery, will reduce the incidence of postoperative deep vein thrombosis in the legs (as measured by the I-125 fibrinogen technique and venography) and of clinical pulmonary embolism. The most widely used dosage has been 5,000 units 2 hours before surgery and 5,000 units every 8 to 12 hours thereafter for 7 days or until the patient is fully ambulatory, whichever is longer. The heparin is given by deep subcutaneous (intrafat, i.e., above the iliac crest or abdominal fat layer, arm or thigh) injection with a fine (25 to 26-gauge) needle to minimize tissue trauma. A concentrated solution of heparin sodium is recommended. Such prophylaxis should be reserved for patients over the age of 40 who are undergoing major surgery. Patients with bleeding disorders and those having brain or spinal cord surgery, spinal anesthesia, eye surgery, or potentially sanguineous operations should be excluded, as should patients receiving oral anticoagulants or platelet-active drugs (see WARNINGS). The value of such prophylaxis in hip surgery has not been established. The possibility of increased bleeding during surgery or postoperatively should be borne in mind. If such bleeding occurs, discontinuance of heparin and neutralization with protamine sulfate are advisable. If clinical evidence of thromboembolism develops despite low-dose prophylaxis, full therapeutic doses of anticoagulants should be given unless contraindicated. Prior to initiating heparinization the physician should rule out bleeding disorders by appropriate history and laboratory tests, and appropriate coagulation tests should be repeated just prior to surgery. Coagulation tests values should be normal or only slightly elevated at these times.

Extracorporeal Dialysis

Follow equipment manufacturers' operating directions carefully.

Blood Transfusion

Addition of 400 to 600 USP units per 100 mL of whole blood is usually employed to prevent coagulation. Usually, 7,500 USP units of heparin sodium are added to 100 mL of 0.9% Sodium Chloride Injection, USP (or 75,000 USP units per 1,000 mL of 0.9% Sodium Chloride Injection, USP) and mixed; from this sterile solution, 6 to 8 mL are added per 100 mL of whole blood.

Laboratory Samples

Addition of 70 to 150 units of heparin sodium per 10 to 20 mL sample of whole blood is usually employed to prevent coagulation of the sample. Leukocyte counts should be performed on heparinized blood within 2 hours after addition of the heparin. Heparinized blood should not be used for isoagglutinin, complement, or erythrocyte fragility tests or platelet counts.

HOW SUPPLIED

Heparin Sodium Injection, USP derived from beef lung is available in the following strengths and package sizes:

1,000 units per mL
10 mL vials |  | NDC 0009-0268-01
25 × 10 mL vials |  | NDC 0009-0268-12
30 mL vials |  | NDC 0009-0268-02
5,000 units per mL
10 mL vials |  | NDC 0009-0291-01
10,000 units per mL
25 × 1 mL vials |  | NDC 0009-0317-10
4 mL vials |  | NDC 0009-0317-02
25 × 4 mL vials |  | NDC 0009-0317-11

Store the product at controlled room temperature 20° to 25°C (68° to 77°F) [see USP].

Rx only

LAB-0116-2.0

Revised April 2006